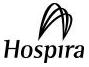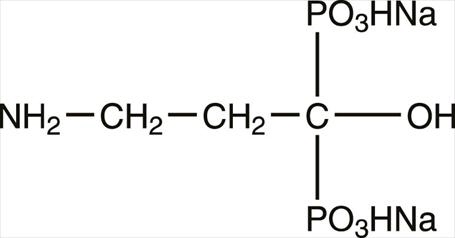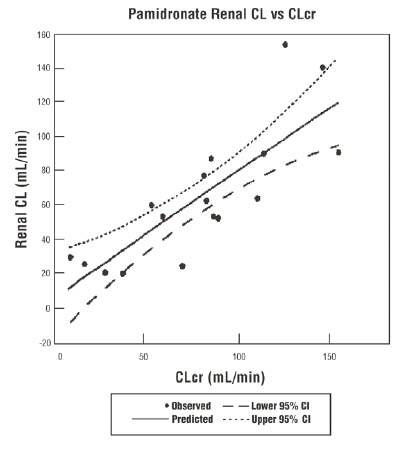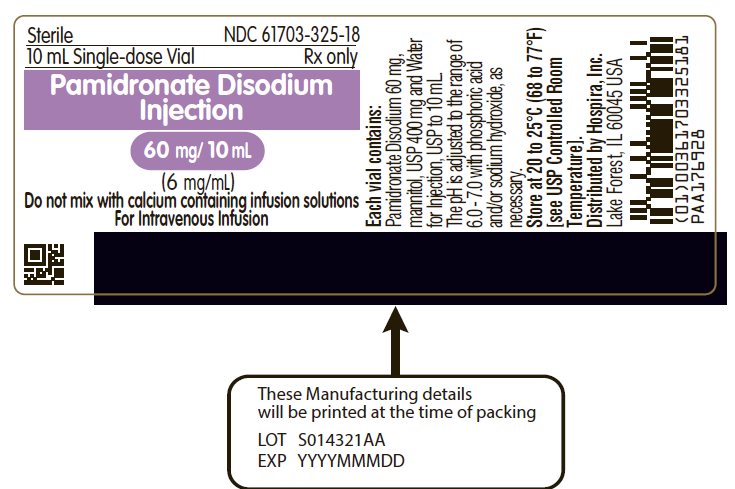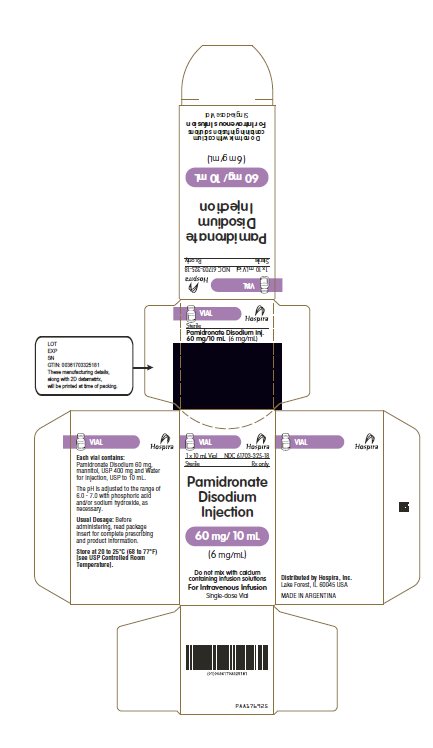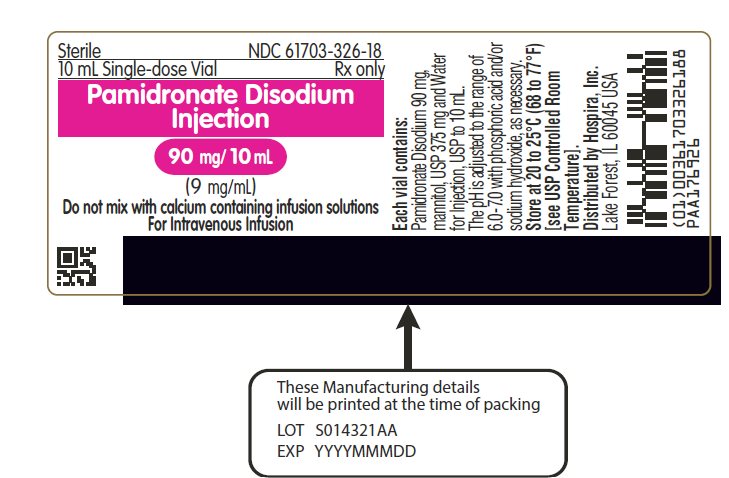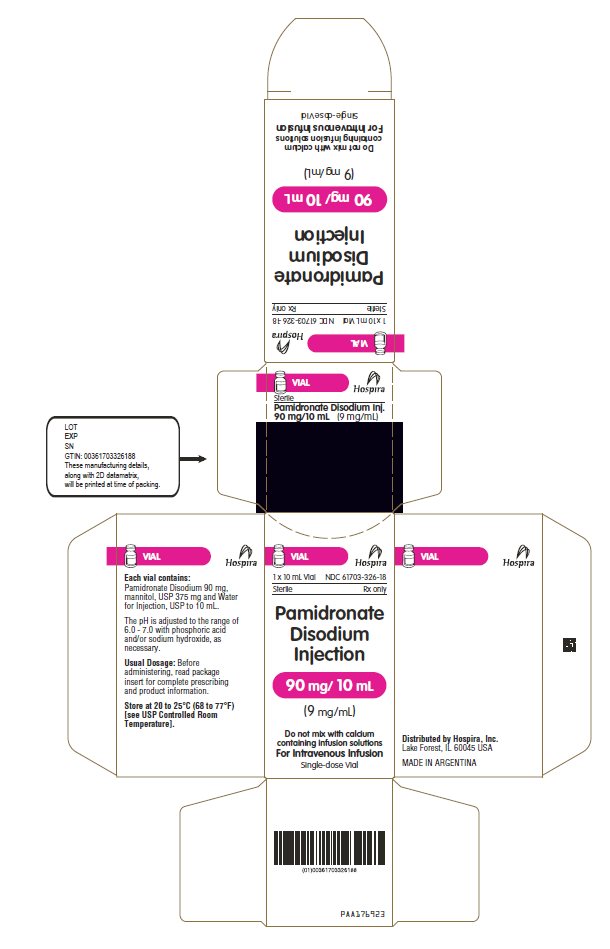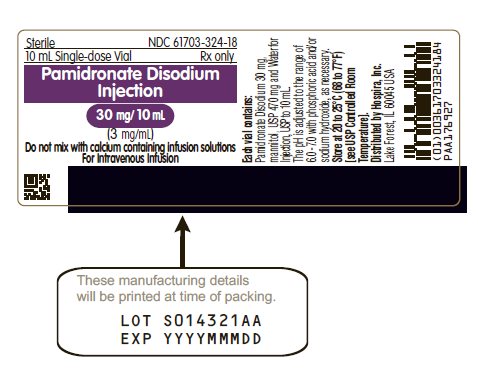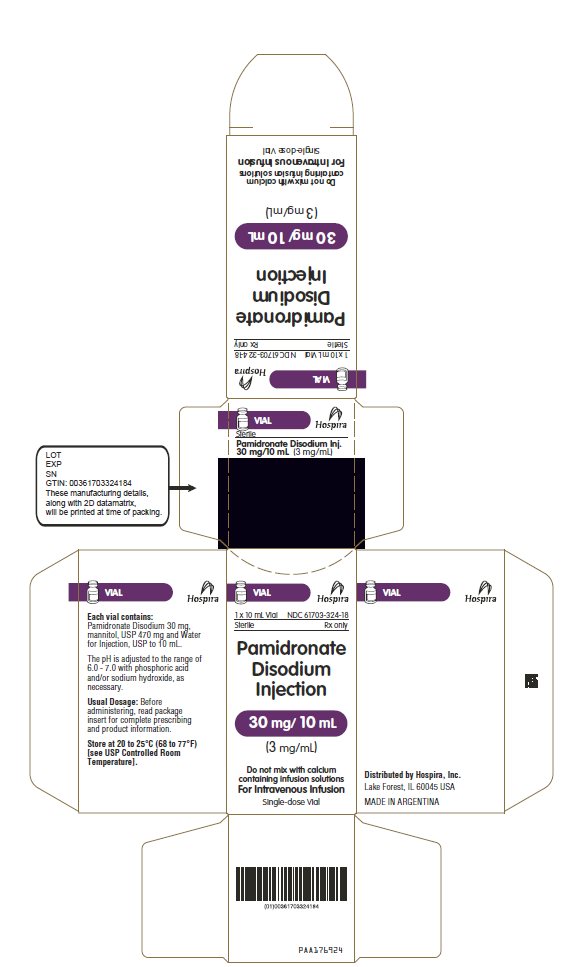 DRUG LABEL: Pamidronate Disodium
NDC: 61703-325 | Form: INJECTION, SOLUTION
Manufacturer: Hospira, Inc.
Category: prescription | Type: HUMAN PRESCRIPTION DRUG LABEL
Date: 20250625

ACTIVE INGREDIENTS: PAMIDRONATE DISODIUM 6 mg/1 mL
INACTIVE INGREDIENTS: MANNITOL 40 mg/1 mL; WATER; PHOSPHORIC ACID; SODIUM HYDROXIDE

Pamidronate Disodium Injection

For Intravenous Infusion

Rx only

Prescribing Information

DESCRIPTION

Pamidronate disodium is a bisphosphonate available in 30 mg, 60 mg, or 90 mg vials for intravenous administration. The pamidronate disodium obtained by combining pamidronic acid and sodium hydroxide is provided in a sterile, ready to use solution for injection. Each mL of the 30 mg vial contains: 3 mg Pamidronate Disodium; 47 mg Mannitol, USP; Water for Injection, USP, q.s.; Phosphoric Acid and/or Sodium Hydroxide, as necessary to adjust pH. Each mL of the 60 mg vial contains: 6 mg Pamidronate Disodium; 40 mg Mannitol, USP; Water for Injection, USP, q.s.; Phosphoric Acid and/or Sodium Hydroxide, as necessary to adjust pH. Each mL of the 90 mg vial contains: 9 mg Pamidronate Disodium; 37.5 mg Mannitol, USP; Water for Injection, USP, q.s.; Phosphoric Acid and/or Sodium Hydroxide, as necessary to adjust pH. The pH of a 1% solution of pamidronate disodium in distilled water is approximately 8.3. Pamidronate, a member of the group of chemical compounds known as bisphosphonates, is an analog of pyrophosphate. Pamidronate disodium is designated chemically as phosphonic acid (3-amino-1-hydroxypropylidene) bis-, disodium salt, and its structural formula is:

Pamidronate disodium is soluble in water and in 2N sodium hydroxide, sparingly soluble in 0.1N hydrochloric acid and in 0.1N acetic acid, and practically insoluble in organic solvents. Its molecular formula is C3H9NO7P2Na2 and its molecular weight is 279.1 (calculated as the anhydrous form).

Inactive Ingredients. Mannitol, USP, Phosphoric Acid and/or Sodium Hydroxide, as necessary (for adjustment to pH range of 6.0 - 7.0) and Water for Injection, USP.

CLINICAL PHARMACOLOGY

The principal pharmacologic action of pamidronate disodium is inhibition of bone resorption. Although the mechanism of antiresorptive action is not completely understood, several factors are thought to contribute to this action. Pamidronate disodium adsorbs to calcium phosphate (hydroxyapatite) crystals in bone and may directly block dissolution of this mineral component of bone. In vitro studies also suggest that inhibition of osteoclast activity contributes to inhibition of bone resorption. In animal studies, at doses recommended for the treatment of hypercalcemia, pamidronate disodium inhibits bone resorption apparently without inhibiting bone formation and mineralization. Of relevance to the treatment of hypercalcemia of malignancy is the finding that pamidronate disodium inhibits the accelerated bone resorption that results from osteoclast hyperactivity induced by various tumors in animal studies.

Pharmacokinetics

Cancer patients (n=24) who had minimal or no bony involvement were given an intravenous infusion of 30, 60, or 90 mg of pamidronate disodium over 4 hours and 90 mg of pamidronate disodium over 24 hours (Table 1).

Distribution

The mean ± SD body retention of pamidronate was calculated to be 54 ± 16% of the dose over 120 hours.

Metabolism

Pamidronate is not metabolized and is exclusively eliminated by renal excretion.

Excretion

After administration of 30, 60, and 90 mg of pamidronate disodium over 4 hours, and 90 mg of pamidronate disodium over 24 hours, an overall mean ± SD of 46 ± 16% of the drug was excreted unchanged in the urine within 120 hours. Cumulative urinary excretion was linearly related to dose. The mean ± SD elimination half-life is 28 ± 7 hours. Mean ± SD total and renal clearances of pamidronate were 107 ± 50 mL/min and 49 ± 28 mL/min, respectively. The rate of elimination from bone has not been determined.

Special Populations

There are no data available on the effects of age, gender, or race on the pharmacokinetics of pamidronate.

Pediatric

Pamidronate is not labeled for use in the pediatric population.

Renal Insufficiency

The pharmacokinetics of pamidronate were studied in cancer patients (n=19) with normal and varying degrees of renal impairment. Each patient received a single 90 mg dose of pamidronate disodium infused over 4 hours. The renal clearance of pamidronate in patients was found to closely correlate with creatinine clearance (see Figure 1). A trend toward a lower percentage of drug excreted unchanged in urine was observed in renally impaired patients. Adverse experiences noted were not found to be related to changes in renal clearance of pamidronate. Given the recommended dose, 90 mg infused over 4 hours, excessive accumulation of pamidronate in renally impaired patients is not anticipated if pamidronate disodium is administered on a monthly basis.

Figure 1: Pamidronate renal clearance as a function of creatinine clearance in patients with normal and impaired renal function.

The lines are the mean prediction line and 95% confidence intervals.

Hepatic Insufficiency

The pharmacokinetics of pamidronate were studied in male cancer patients at risk for bone metastases with normal hepatic function (n=6) and mild to moderate hepatic dysfunction (n=7). Each patient received a single 90 mg dose of pamidronate disodium infused over 4 hours. Although there was a statistically significant difference in the pharmacokinetics between patients with normal and impaired hepatic function, the difference was not considered clinically relevant. Patients with hepatic impairment exhibited higher mean AUC (53%) and Cmax (29%), and decreased plasma clearance (33%) values. Nevertheless, pamidronate was still rapidly cleared from the plasma. Drug levels were not detectable in patients by 12 to 36 hours after drug infusion. Because pamidronate disodium is administered on a monthly basis, drug accumulation is not expected. No changes in pamidronate disodium dosing regimen are recommended for patients with mild to moderate abnormal hepatic function. Pamidronate disodium has not been studied in patients with severe hepatic impairment.

Drug-Drug Interactions

There are no human pharmacokinetic data for drug interactions with pamidronate disodium.

Table 1 Mean (SD, CV%) Pamidronate Pharmacokinetic Parameters in Cancer Patients (n=6 for each group)
Dose (infusion rate) | Maximum Concentration (mcg/mL) | Percent of dose excreted in urine | Total Clearance (mL/min) | Renal Clearance (mL/min)
30 mg (4 hrs) | 0.73 (0.14, 19.1%) | 43.9 (14.0, 31.9%) | 136 (44, 32.4%) | 58 (27, 46.5%)
60 mg (4 hrs) | 1.44 (0.57, 39.6%) | 47.4 (47.4, 54.4%) | 88 (56, 63.6%) | 42 (28, 66.7%)
90 mg (4 hrs) | 2.61 (0.74, 28.3%) | 45.3 (25.8, 56.9%) | 103 (37, 35.9%) | 44 (16, 36.4%)
90 mg (24 hrs) | 1.38 (1.97, 142.7%) | 47.5 (10.2, 21.5%) | 101 (58, 57.4%) | 52 (42, 80.8%)

After intravenous administration of radiolabeled pamidronate in rats, approximately 50% to 60% of the compound was rapidly adsorbed by bone and slowly eliminated from the body by the kidneys. In rats given 10 mg/kg bolus injections of radiolabeled pamidronate disodium, approximately 30% of the compound was found in the liver shortly after administration and was then redistributed to bone or eliminated by the kidneys over 24 to 48 hours. Studies in rats injected with radiolabeled pamidronate disodium showed that the compound was rapidly cleared from the circulation and taken up mainly by bones, liver, spleen, teeth, and tracheal cartilage. Radioactivity was eliminated from most soft tissues within 1 to 4 days; was detectable in liver and spleen for 1 and 3 months, respectively; and remained high in bones, trachea, and teeth for 6 months after dosing. Bone uptake occurred preferentially in areas of high bone turnover. The terminal phase of elimination half-life in bone was estimated to be approximately 300 days.

Pharmacodynamics

Serum phosphate levels have been noted to decrease after administration of pamidronate disodium, presumably because of decreased release of phosphate from bone and increased renal excretion as parathyroid hormone levels, which are usually suppressed in hypercalcemia associated with malignancy, return toward normal. Phosphate therapy was administered in 30% of the patients in response to a decrease in serum phosphate levels. Phosphate levels usually returned toward normal within 7 to 10 days.

Urinary calcium/creatinine and urinary hydroxyproline/creatinine ratios decrease and usually return to within or below normal after treatment with pamidronate disodium. These changes occur within the first week after treatment, as do decreases in serum calcium levels, and are consistent with an antiresorptive pharmacologic action.

Hypercalcemia of Malignancy

Osteoclastic hyperactivity resulting in excessive bone resorption is the underlying pathophysiologic derangement in metastatic bone disease and hypercalcemia of malignancy. Excessive release of calcium into the blood as bone is resorbed results in polyuria and gastrointestinal disturbances, with progressive dehydration and decreasing glomerular filtration rate. This, in turn, results in increased renal resorption of calcium, setting up a cycle of worsening systemic hypercalcemia. Correction of excessive bone resorption and adequate fluid administration to correct volume deficits are therefore essential to the management of hypercalcemia.

Most cases of hypercalcemia associated with malignancy occur in patients who have breast cancer; squamous-cell tumors of the lung or head and neck; renal-cell carcinoma; and certain hematologic malignancies, such as multiple myeloma and some types of lymphomas. A few less-common malignancies, including vasoactive intestinal-peptide-producing tumors and cholangiocarcinoma, have a high incidence of hypercalcemia as a metabolic complication. Patients who have hypercalcemia of malignancy can generally be divided into two groups, according to the pathophysiologic mechanism involved.

In humoral hypercalcemia, osteoclasts are activated and bone resorption is stimulated by factors such as parathyroid-hormone-related protein, which are elaborated by the tumor and circulate systemically. Humoral hypercalcemia usually occurs in squamous-cell malignancies of the lung or head and neck or in genitourinary tumors such as renal-cell carcinoma or ovarian cancer. Skeletal metastases may be absent or minimal in these patients.

Extensive invasion of bone by tumor cells can also result in hypercalcemia due to local tumor products that stimulate bone resorption by osteoclasts. Tumors commonly associated with locally mediated hypercalcemia include breast cancer and multiple myeloma.

Total serum calcium levels in patients who have hypercalcemia of malignancy may not reflect the severity of hypercalcemia, since concomitant hypoalbuminemia is commonly present. Ideally, ionized calcium levels should be used to diagnose and follow hypercalcemic conditions; however, these are not commonly or rapidly available in many clinical situations. Therefore, adjustment of the total serum calcium value for differences in albumin levels is often used in place of measurement of ionized calcium; several nomograms are in use for this type of calculation (see DOSAGE AND ADMINISTRATION).

Clinical Trials

In one double-blind clinical trial, 52 patients who had hypercalcemia of malignancy were enrolled to receive 30 mg, 60 mg, or 90 mg of pamidronate disodium as a single 24-hour intravenous infusion if their corrected serum calcium levels were ≥ 12.0 mg/dL after 48 hours of saline hydration.

The mean baseline-corrected serum calcium for the 30 mg, 60 mg, and 90 mg groups were 13.8 mg/dL, 13.8 mg/dL, and 13.3 mg/dL, respectively. The majority of patients (64%) had decreases in albumin-corrected serum calcium levels by 24 hours after initiation of treatment. Mean-corrected serum calcium levels at days 2 to 7 after initiation of treatment with pamidronate disodium were significantly reduced from baseline in all three dosage groups. As a result, by 7 days after initiation of treatment with pamidronate disodium, 40%, 61%, and 100% of the patients receiving 30 mg, 60 mg, and 90 mg of pamidronate disodium, respectively, had normal-corrected serum calcium levels. Many patients (33% to 53%) in the 60 mg and 90 mg dosage groups continued to have normal-corrected serum calcium levels, or a partial response (≥ 15% decrease of corrected serum calcium from baseline), at Day 14.

In a second double-blind, controlled clinical trial, 65 cancer patients who had corrected serum calcium levels of ≥ 12.0 mg/dL after at least 24 hours of saline hydration were randomized to receive either 60 mg of pamidronate disodium as a single 24-hour intravenous infusion or 7.5 mg/kg of etidronate disodium as a 2-hour intravenous infusion daily for 3 days. Thirty patients were randomized to receive pamidronate disodium and 35 to receive etidronate disodium.

The mean baseline-corrected serum calcium for the pamidronate disodium 60 mg and etidronate disodium groups were 14.6 mg/dL and 13.8 mg/dL, respectively.

By Day 7, 70% of the patients in the pamidronate disodium group and 41% of the patients in the etidronate disodium group had normal-corrected serum calcium levels (P<0.05). When partial responders (≥15% decrease of serum calcium from baseline) were also included, the response rates were 97% for the pamidronate disodium group and 65% for the etidronate disodium group (P<0.01). Mean-corrected serum calcium for the pamidronate disodium and etidronate disodium groups decreased from baseline values to 10.4 and 11.2 mg/dL, respectively, on Day 7. At Day 14, 43% of patients in the pamidronate disodium group and 18% of patients in the etidronate disodium group still had normal-corrected serum calcium levels, or maintenance of a partial response. For responders in the pamidronate disodium and etidronate disodium groups, the median duration of response was similar (7 and 5 days, respectively). The time course of effect on corrected serum calcium is summarized in the following table.

Change in Corrected Serum Calcium by Time from Initiation of Treatment
Time (hr) | Mean Change from Baseline in Corrected Serum Calcium (mg/dL)
 | Pamidronate Disodium | Etidronate Disodium | P-value [Comparison between treatment groups.]
Baseline | 14.6 | 13.8
24 | -0.3 | -0.5
48 | -1.5 | -1.1
72 | -2.6 | -2.0
96 | -3.5 | -2.0 | <0.01
168 | -4.1 | -2.5 | <0.01

In a third multicenter, randomized, parallel double-blind trial, a group of 69 cancer patients with hypercalcemia was enrolled to receive 60 mg of pamidronate disodium as a 4- or 24-hour infusion, which was compared to a saline-treatment group. Patients who had a corrected serum calcium level of ≥ 12.0 mg/dL after 24 hours of saline hydration were eligible for this trial.

The mean baseline-corrected serum calcium levels for pamidronate disodium 60 mg 4-hour infusion, pamidronate disodium 60 mg 24-hour infusion, and saline infusion were 14.2 mg/dL, 13.7 mg/dL, and 13.7 mg/dL, respectively.

By Day 7 after initiation of treatment, 78%, 61%, and 22% of the patients had normal-corrected serum calcium levels for the 60 mg 4-hour infusion, 60 mg 24-hour infusion, and saline infusion, respectively. At Day 14, 39% of the patients in the pamidronate disodium 60 mg 4-hour infusion group and 26% of the patients in the pamidronate disodium 60 mg 24-hour infusion group had normal-corrected serum calcium levels or maintenance of a partial response.

For responders, the median duration of complete responses was 4 days and 6.5 days for pamidronate disodium 60 mg 4-hour infusion and pamidronate disodium 60 mg 24-hour infusion, respectively.

In all three trials, patients treated with pamidronate disodium had similar response rates in the presence or absence of bone metastases. Concomitant administration of furosemide did not affect response rates.

Thirty-two patients who had recurrent or refractory hypercalcemia of malignancy were given a second course of 60 mg of pamidronate disodium over a 4- or 24-hour period. Of these, 41% showed a complete response and 16% showed a partial response to the retreatment, and these responders had about a 3 mg/dL fall in mean-corrected serum calcium levels 7 days after retreatment.

In a fourth multicenter, randomized, double-blind trial, 103 patients with cancer and hypercalcemia (corrected serum calcium ≥ 12.0 mg/dL) received 90 mg of pamidronate disodium as a 2-hour infusion. The mean baseline corrected serum calcium was 14.0 mg/dL. Patients were not required to receive intravenous hydration prior to drug administration, but all subjects did receive at least 500 mL of intravenous saline hydration concomitantly with the pamidronate infusion. By Day 10 after drug infusion, 70% of patients had normal corrected serum calcium levels (<10.8 mg/dL).

Paget’s Disease

Paget’s disease of bone (osteitis deformans) is an idiopathic disease characterized by chronic, focal areas of bone destruction complicated by concurrent excessive bone repair, affecting one or more bones. These changes result in thickened but weakened bones that may fracture or bend under stress. Signs and symptoms may be bone pain, deformity, fractures, neurological disorders resulting from cranial and spinal nerve entrapment and from spinal cord and brain stem compression, increased cardiac output to the involved bone, increased serum alkaline phosphatase levels (reflecting increased bone formation) and/or urine hydroxyproline excretion (reflecting increased bone resorption).

Clinical Trials

In one double-blind clinical trial, 64 patients with moderate to severe Paget’s disease of bone were enrolled to receive 5 mg, 15 mg, or 30 mg of pamidronate disodium as a single 4-hour infusion on 3 consecutive days, for total doses of 15 mg, 45 mg, and 90 mg of pamidronate disodium.

The mean baseline serum alkaline phosphatase levels were 1409 U/L, 983 U/L, and 1085 U/L, and the mean baseline urine hydroxyproline/creatinine ratios were 0.25, 0.19, and 0.19 for the 15 mg, 45 mg, and 90 mg groups, respectively.

The effects of pamidronate disodium on serum alkaline phosphatase (SAP) and urine hydroxyproline/creatinine ratios (UOHP/C) are summarized in the following table:

Percent of Patients with Significant % Decreases in SAP and UOHP/C
SAP |  |  |  | UOHP/C
% Decrease | 15 mg | 45 mg | 90 mg | 15 mg | 45 mg | 90 mg
≥50 | 26 | 33 | 60 | 15 | 47 | 72
≥30 | 40 | 65 | 83 | 35 | 57 | 85

The median maximum percent decreases from baseline in serum alkaline phosphatase and urine hydroxyproline/creatinine ratios were 25%, 41%, and 57%, and 25%, 47% and 61% for the 15 mg, 45 mg, and 90 mg groups, respectively. The median time to response (≥ 50% decrease) for serum alkaline phosphatase was approximately 1 month for the 90 mg group, and the response duration ranged from 1 to 372 days.

No statistically significant differences between treatment groups, or statistically significant changes from baseline were observed for the bone pain response, mobility, and global evaluation in the 45 mg and 90 mg groups. Improvement in radiologic lesions occurred in some patients in the 90 mg group.

Twenty-five patients who had Paget’s disease were retreated with 90 mg of pamidronate disodium. Of these, 44% had a ≥ 50% decrease in serum alkaline phosphatase from baseline after treatment, and 39% had a ≥ 50% decrease in urine hydroxyproline/creatinine ratio from baseline after treatment.

Osteolytic Bone Metastases of Breast Cancer and Osteolytic Lesions of Multiple Myeloma

Osteolytic bone metastases commonly occur in patients with multiple myeloma or breast cancer. These cancers demonstrate a phenomenon known as osteotropism, meaning they possess an extraordinary affinity for bone. The distribution of osteolytic bone metastases in these cancers is predominantly in the axial skeleton, particularly the spine, pelvis, and ribs, rather than the appendicular skeleton, although lesions in the proximal femur and humerus are not uncommon. This distribution is similar to the red bone marrow in which slow blood flow possibly assists attachment of metastatic cells. The surface-to-volume ratio of trabecular bone is much higher than cortical bone, and therefore disease processes tend to occur more floridly in trabecular bone than at sites of cortical tissue.

These bone changes can result in patients having evidence of osteolytic skeletal destruction leading to severe bone pain that requires either radiation therapy or narcotic analgesics (or both) for symptomatic relief. These changes also cause pathologic fractures of bone in both the axial and appendicular skeleton. Axial skeletal fractures of the vertebral bodies may lead to spinal cord compression or vertebral body collapse with significant neurologic complications. Also, patients may experience episode(s) of hypercalcemia.

Clinical Trials

In a double-blind, randomized, placebo-controlled trial, 392 patients with advanced multiple myeloma were enrolled to receive pamidronate disodium or placebo in addition to their underlying antimyeloma therapy to determine the effect of pamidronate disodium on the occurrence of skeletal-related events (SREs). SREs were defined as episodes of pathologic fractures, radiation therapy to bone, surgery to bone, and spinal cord compression. Patients received either 90 mg of pamidronate disodium or placebo as a monthly 4-hour intravenous infusion for 9 months. Of the 392 patients, 377 were evaluable for efficacy (196 pamidronate disodium, 181 placebo). The proportion of patients developing any SRE was significantly smaller in the pamidronate disodium group (24% vs 41%, P<0.001), and the mean skeletal morbidity rate (#SRE/year) was significantly smaller for pamidronate disodium patients than for placebo patients (mean: 1.1 vs 2.1, P<.02). The times to the first SRE occurrence, pathologic fracture, and radiation to bone were significantly longer in the pamidronate disodium group (P=.001, .006, and .046, respectively). Moreover, fewer pamidronate disodium patients suffered any pathologic fracture (17% vs 30%, P=.004) or needed radiation to bone (14% vs 22%, P=.049).

In addition, decreases in pain scores from baseline occurred at the last measurement for those pamidronate disodium patients with pain at baseline (P=.026) but not in the placebo group. At the last measurement, a worsening from baseline was observed in the placebo group for the Spitzer quality of life variable (P<.001) and ECOG performance status (P<.011) while there was no significant deterioration from baseline in these parameters observed in pamidronate disodium-treated patients.*

After 21 months, the proportion of patients experiencing any skeletal event remained significantly smaller in the pamidronate disodium group than the placebo group (P=.015). In addition, the mean skeletal morbidity rate (#SRE/year) was 1.3 vs 2.2 for pamidronate disodium patients vs placebo patients (P=.008), and time to first SRE was significantly longer in the pamidronate disodium group compared to placebo (P=.016). Fewer pamidronate disodium patients suffered vertebral pathologic fractures (16% vs 27%, P=.005). Survival of all patients was not different between treatment groups.

Two double-blind, randomized, placebo-controlled trials compared the safety and efficacy of 90 mg of pamidronate disodium infused over 2 hours every 3 to 4 weeks for 24 months to that of placebo in preventing SREs in breast cancer patients with osteolytic bone metastases who had one or more predominantly lytic metastases of at least 1 cm in diameter: one in patients being treated with antineoplastic chemotherapy and the second in patients being treated with hormonal antineoplastic therapy at trial entry.

382 patients receiving chemotherapy were randomized, 185 to pamidronate disodium and 197 to placebo. 372 patients receiving hormonal therapy were randomized, 182 to pamidronate disodium and 190 to placebo. All but three patients were evaluable for efficacy. Patients were followed for 24 months of therapy or until they went off study. Median duration of follow-up was 13 months in patients receiving chemotherapy and 17 months in patients receiving hormone therapy. Twenty-five percent of the patients in the chemotherapy study and 37% of the patients in the hormone therapy study received pamidronate disodium for 24 months. The efficacy results are shown in the table below:

 | Breast Cancer Patients Receiving Chemotherapy |  |  |  |  |  | Breast Cancer Patients Receiving Hormonal Therapy
 | Any SRE |  | Radiation |  | Fractures |  | Any SRE |  | Radiation |  | Fractures
N | PD 185 | P 195 | PD 185 | P 195 | PD 185 | P 195 | PD 182 | P 189 | PD 182 | P 189 | PD 182 | P 189
Skeletal Morbidity Rate (#SRE/Year) Mean | 2.5 | 3.7 | 0.8 | 1.3 | 1.6 | 2.2 | 2.4 | 3.6 | 0.6 | 1.2 | 1.6 | 2.2
P-value | <.001 |  | <.001 [Fractures and radiation to bone were two of several secondary endpoints. The statistical significance of these analyses may be overestimated since numerous analyses were performed.] |  | .018 |  | .021 |  | .013 |  | .040
Proportion of Patients having an SRE | 46% | 65% | 28% | 45% | 36% | 49% | 55% | 63% | 31% | 40% | 45% | 55%
P-value | <.001 |  | <.001 |  | .014 |  | 0.094 |  | .058 |  | .054
Median Time to SRE (months) | 13.9 | 7.0 | NR [NR = Not Reached.] | 14.2 | 25.8 | 13.3 | 10.9 | 7.4 | NR | 23.4 | 20.6 | 12.8
P-value | <.001 |  | <.001 |  | .009 |  | 0.118 |  | .016 |  | .113

Bone lesion response was radiographically assessed at baseline and at 3, 6, and 12 months. The complete + partial response rate was 33% in pamidronate disodium patients and 18% in placebo patients treated with chemotherapy (P=.001). No difference was seen between pamidronate disodium and placebo in hormonally-treated patients.

Pain and analgesic scores, ECOG performance status and Spitzer quality of life index were measured at baseline and periodically during the trials. The changes from baseline to the last measurement carried forward are shown in the following table:

Mean Change (Δ) from Baseline at Last Measurement
 | Breast Cancer Patients Receiving Chemotherapy |  |  |  |  | Breast Cancer Patients Receiving Hormonal Therapy
 | Pamidronate Disodium |  | Placebo |  | PD vs P | Pamidronate Disodium |  | Placebo |  | PD vs P
 | N | MeanΔ | N | MeanΔ | P-value [The statistical significance of analyses of these secondary endpoints of pain, quality of life, and performance status in all three trials may be overestimated since numerous analyses were performed.] | N | MeanΔ | N | MeanΔ | P-value
Pain Score | 175 | +0.93 | 183 | +1.69 | .050 | 173 | +0.50 | 179 | +1.60 | .007
Analgesic Score | 175 | +0.74 | 183 | +1.55 | .009 | 173 | +0.90 | 179 | +2.28 | <.001
ECOG PS | 178 | +0.81 | 186 | +1.19 | .002 | 175 | +0.95 | 182 | +0.90 | .773
Spitzer QOL | 177 | -1.76 | 185 | -2.21 | .103 | 173 | -1.86 | 181 | -2.05 | .409
Decreases in pain, analgesic scores and ECOG PS, and increases in Spitzer QOL indicate an improvement from baseline.

INDICATIONS AND USAGE

Hypercalcemia of Malignancy

Pamidronate disodium, in conjunction with adequate hydration, is indicated for the treatment of moderate or severe hypercalcemia associated with malignancy, with or without bone metastases.

Patients who have either epidermoid or non-epidermoid tumors respond to treatment with pamidronate disodium. Vigorous saline hydration, an integral part of hypercalcemia therapy, should be initiated promptly and an attempt should be made to restore the urine output to about 2 L/day throughout treatment. Mild or asymptomatic hypercalcemia may be treated with conservative measures (i.e., saline hydration, with or without loop diuretics). Patients should be hydrated adequately throughout the treatment, but overhydration, especially in those patients who have cardiac failure, must be avoided. Diuretic therapy should not be employed prior to correction of hypovolemia. The safety and efficacy of pamidronate disodium in the treatment of hypercalcemia associated with hyperparathyroidism or with other non-tumor-related conditions has not been established.

Paget’s Disease

Pamidronate disodium is indicated for the treatment of patients with moderate to severe Paget’s disease of bone. The effectiveness of pamidronate disodium was demonstrated primarily in patients with serum alkaline phosphatase ≥ 3 times the upper limit of normal. Pamidronate disodium therapy in patients with Paget’s disease has been effective in reducing serum alkaline phosphatase and urinary hydroxyproline levels by ≥ 50% in at least 50% of patients, and by ≥ 30% in at least 80% of patients. Pamidronate disodium therapy has also been effective in reducing these biochemical markers in patients with Paget’s disease who failed to respond, or no longer responded to other treatments.

Osteolytic Bone Metastases of Breast Cancer and Osteolytic Lesions of Multiple Myeloma

Pamidronate disodium is indicated, in conjunction with standard antineoplastic therapy, for the treatment of osteolytic bone metastases of breast cancer and osteolytic lesions of multiple myeloma. The pamidronate disodium treatment effect appeared to be smaller in the study of breast cancer patients receiving hormonal therapy than in the study of those receiving chemotherapy, however, overall evidence of clinical benefit has been demonstrated (see CLINICAL PHARMACOLOGY, Osteolytic Bone Metastases of Breast Cancer and Osteolytic Lesions of Multiple Myeloma, Clinical Trials section).

CONTRAINDICATIONS

Pamidronate disodium is contraindicated in patients with clinically significant hypersensitivity to pamidronate disodium or other bisphosphonates.

WARNINGS

Deterioration in Renal Function

Bisphosphonates, including pamidronate disodium, have been associated with renal toxicity manifested as deterioration of renal function and potential renal failure.

DUE TO THE RISK OF CLINICALLY SIGNIFICANT DETERIORATION IN RENAL FUNCTION, WHICH MAY PROGRESS TO RENAL FAILURE, SINGLE DOSES OF PAMIDRONATE DISODIUM SHOULD NOT EXCEED 90 MG (see DOSAGE AND ADMINISTRATION for appropriate infusion durations). Renal deterioration, progression to renal failure, and dialysis have been reported in patients after the initial or a single dose of pamidronate disodium.

Focal segmental glomerulosclerosis (including the collapsing variant) with or without nephrotic syndrome, which may lead to renal failure, has been reported in pamidronate disodium-treated patients, particularly in the setting of multiple myeloma and breast cancer. Some of these patients had gradual improvement in renal status after pamidronate disodium was discontinued.

Patients who receive pamidronate disodium should have serum creatinine assessed prior to each treatment. Patients treated with pamidronate disodium for bone metastases should have the dose withheld if renal function has deteriorated (see DOSAGE AND ADMINISTRATION).

PREGNANCY:

Bisphosphonates, such as pamidronate disodium, are incorporated into the bone matrix, from where they are gradually released over periods of weeks to years. Pamidronate disodium may cause fetal harm when administered to a pregnant woman. In reproductive studies in rats and rabbits, pamidronate doses equivalent to 0.6 to 8.3 times the highest human recommended dose resulted in maternal toxicity and embryo/fetal effects. There are no adequate and well-controlled studies of pamidronate disodium in pregnant women. If this drug is used during pregnancy, or if the patient becomes pregnant while taking this drug, apprise the patient of the potential hazard to the fetus (See PRECAUTIONS).

PRECAUTIONS

General

Standard hypercalcemia-related metabolic parameters, such as serum levels of calcium, phosphate, magnesium, and potassium, should be carefully monitored following initiation of therapy with pamidronate disodium. Cases of asymptomatic hypophosphatemia (12%), hypokalemia (7%), hypomagnesemia (11%), and hypocalcemia (5% to 12%), were reported in pamidronate disodium-treated patients. Rare cases of symptomatic hypocalcemia (including tetany) have been reported in association with pamidronate therapy. If hypocalcemia occurs, short-term calcium therapy may be necessary. In Paget’s disease of bone, 17% of patients treated with 90 mg of pamidronate disodium showed serum calcium levels below 8 mg/dL.

Patients with a history of thyroid surgery may have relative hypoparathyroidism that may predispose to hypocalcemia with pamidronate disodium.

Renal Insufficiency

Pamidronate disodium is excreted intact primarily via the kidney, and the risk of renal adverse reactions may be greater in patients with impaired renal function. Patients who receive pamidronate disodium should have serum creatinine assessed prior to each treatment. In patients receiving pamidronate disodium for bone metastases, who show evidence of deterioration in renal function, pamidronate disodium treatment should be withheld until renal function returns to baseline (see WARNINGS and DOSAGE AND ADMINISTRATION).

In clinical trials, patients with renal impairment (serum creatinine >3.0 mg/dL) have not been studied. Limited pharmacokinetic data exist in patients with creatinine clearance <30 mL/min (See Clinical Pharmacology, Pharmacokinetics). For the treatment of bone metastases, the use of pamidronate disodium in patients with severe renal impairment is not recommended. In other indications, clinical judgment should determine whether the potential benefit outweighs the potential risk in such patients.

Osteonecrosis of the Jaw

Osteonecrosis of the jaw (ONJ) has been reported predominantly in cancer patients treated with intravenous bisphosphonates, including pamidronate disodium. Many of these patients were also receiving chemotherapy and corticosteroids which may be risk factors for ONJ. Post-marketing experience and the literature suggest a greater frequency of reports of ONJ based on tumor type (advanced breast cancer, multiple myeloma), and dental status (dental extraction, periodontal disease, local trauma including poorly fitting dentures). Many reports of ONJ involved patients with signs of local infection including osteomyelitis.

Cancer patients should maintain good oral hygiene and should have a dental examination with preventive dentistry prior to treatment with bisphosphonates.

While on treatment, these patients should avoid invasive dental procedures if possible. For patients who develop ONJ while on bisphosphonate therapy, dental surgery may exacerbate the condition. For patients requiring dental procedures, there are no data available to suggest whether discontinuation of bisphosphonate treatment reduces the risk of ONJ. Clinical judgment of the treating physician should guide the management plan of each patient based on individual benefit/risk assessment (see ADVERSE REACTIONS).

Musculoskeletal Pain

In post-marketing experience, severe and occasionally incapacitating bone, joint, and/or muscle pain has been reported in patients taking bisphosphonates. This category of drugs includes pamidronate disodium. The time to onset of symptoms varied from one day to several months after starting the drug. Most patients had relief of symptoms after stopping. A subset had recurrence of symptoms when rechallenged with the same drug or another bisphosphonate.

Atypical fractures of the femur

Atypical subtrochanteric and diaphyseal femoral fractures have been reported in patients receiving bisphosphonate therapy, including pamidronate disodium. These fractures can occur anywhere in the femoral shaft from just below the lesser trochanter to just above the supracondylar flare and are transverse or short oblique in orientation without evidence of comminution. These fractures occur after minimal or no trauma. Patients may experience thigh or groin pain weeks to months before presenting with a completed femoral fracture. Fractures are often bilateral; therefore the contralateral femur should be examined in bisphosphonate-treated patients who have sustained a femoral shaft fracture. Poor healing of these fractures has also been reported. A number of case reports noted that patients were also receiving treatment with glucocorticoids (such as prednisone or dexamethasone) at the time of fracture. Causality with bisphosphonate therapy has not been established.

Any patient with a history of bisphosphonate exposure who presents with thigh or groin pain in the absence of trauma should be suspected of having an atypical fracture and should be evaluated. Discontinuation of pamidronate disodium therapy in patients suspected to have an atypical femur fracture should be considered pending evaluation of the patient, based on an individual benefit risk assessment. It is unknown whether the risk of atypical femur fracture continues after stopping therapy.

Laboratory Tests

Patients who receive pamidronate disodium should have serum creatinine assessed prior to each treatment. Serum calcium, electrolytes, phosphate, magnesium, and CBC, differential, and hematocrit/hemoglobin must be closely monitored in patients treated with pamidronate disodium. Patients who have preexisting anemia, leukopenia, or thrombocytopenia should be monitored carefully in the first 2 weeks following treatment. Patients receiving pamidronate disodium may be at risk for anemia, leukopenia or thrombocytopenia and should have regular hematology assessments.

Drug Interactions

Concomitant administration of a loop diuretic had no effect on the calcium-lowering action of pamidronate disodium.

Caution is indicated when pamidronate disodium is used with other potentially nephrotoxic drugs.

In multiple myeloma patients, the risk of renal function deterioration may be increased when pamidronate disodium is used in combination with thalidomide.

Carcinogenesis, Mutagenesis, Impairment of Fertility

In a 104-week carcinogenicity study with daily oral administration of pamidronate in rats, there was a positive dose response relationship for benign adrenal pheochromocytoma in males (P <0.00001). Although this condition was also observed in females, the incidence was not statistically significant. When the dose calculations were adjusted to account for the limited oral bioavailability of pamidronate in rats, systemic exposure with the lowest daily dose associated with adrenal pheochromocytoma resulted in systemic exposures that were similar to the systemic exposure achieved at the intended clinical dose.

Adrenal pheochromocytoma was also observed in low numbers in the control animals and is considered a relatively common spontaneous neoplasm in the rat. Pamidronate given daily by oral administration was not carcinogenic in an 80-week study in mice.

Pamidronate was nonmutagenic in six mutagenicity assays, including: Ames bacterial mutagenicity assay, (with and without metabolic activation), nucleus-anomaly test, sister-chromatid-exchange study, point-mutation test, and micronucleus test in the rat.

In rats, decreased fertility occurred in first-generation offspring of parents who had received 150 mg/kg of pamidronate orally; however, this occurred only when animals were mated with members of the same dose group. Pamidronate has not been administered intravenously in such a study.

Animal Toxicology

In both rats and dogs, nephropathy has been associated with intravenous (bolus and infusion) administration of pamidronate.

Two 7-day intravenous infusion studies were conducted in the dog wherein pamidronate was given for 1, 4, or 24 hours at doses of 1 to 20 mg/kg for up to 7 days. In the first study, the compound was well tolerated at 3 mg/kg (1.7 x highest recommended human dose [HRHD] for a single intravenous infusion) when administered for 4 or 24 hours, but renal findings such as elevated BUN and creatinine levels and renal tubular necrosis occurred when 3 mg/kg was infused for 1 hour and at doses of ≥10 mg/kg. In the second study, slight renal tubular necrosis was observed in 1 male at 1 mg/kg when infused for 4 hours. Additional findings included elevated BUN levels in several treated animals and renal tubular dilation and/or inflammation at ≥1 mg/kg after each infusion time.

Pamidronate was given to rats at doses of 2, 6, and 20 mg/kg and to dogs at doses of 2, 4, 6, and 20 mg/kg as a 1-hour infusion, once a week, for 3 months followed by a 1-month recovery period. In rats, nephrotoxicity was observed at ≥6 mg/kg and included increased BUN and creatinine levels and tubular degeneration and necrosis. These findings were still present at 20 mg/kg at the end of the recovery period. In dogs, moribundity/death and renal toxicity occurred at 20 mg/kg as did kidney findings of elevated BUN and creatinine levels at ≥6 mg/kg and renal tubular degeneration at ≥4 mg/kg. The kidney changes were partially reversible at 6 mg/kg. In both studies, the dose level that produced no adverse renal effects was considered to be 2 mg/kg (1.1 x HRHD for a single intravenous infusion).

Pregnancy (See WARNINGS)

There are no adequate and well-controlled studies in pregnant women. Pamidronate disodium may cause fetal harm when administered to a pregnant woman. Bisphosphonates, such as pamidronate disodium, are incorporated into the bone matrix, from where they are gradually released over periods of weeks to years. The extent of bisphosphonate incorporation into adult bone, and hence, the amount available for release back into the systemic circulation, is directly related to the total dose and duration of bisphosphonate use. Although there are no data on fetal risk in humans, bisphosphonates do cause fetal harm in animals, and animal data suggest that uptake of bisphosphonates into fetal bone is greater than into maternal bone. Therefore, there is a theoretical risk of fetal harm (e.g. skeletal and other abnormalities) if a woman becomes pregnant after completing a course of bisphosphonate therapy. The impact of variables such as time between cessation of bisphosphonate therapy to conception, the particular bisphosphonate used, and the route of administration (intravenous versus oral) on this risk has not been established. If pamidronate disodium is used during pregnancy or if the patient becomes pregnant while taking or after taking this drug, the patient should be apprised of the potential hazard to the fetus.

Intravenous bolus dosing of pregnant rats and rabbits with pamidronate resulted in maternal toxicity and embryo/fetal effects when given during organogenesis at doses of 0.6 to 8.3 times the highest recommended human dose for a single intravenous infusion. Pamidronate can cross the placenta in rats and has produced marked maternal and nonteratogenic embryo/fetal effects in both rats and rabbits.

Nursing Mothers

It is not known whether pamidronate is excreted in human milk. Because many drugs are excreted in human milk, and because of the potential for serious adverse reactions in nursing infants from pamidronate disodium, a decision should be made to discontinue nursing or to discontinue the drug, taking into account the importance of the drug to the mother.

Pediatric Use

Safety and effectiveness of pamidronate disodium in pediatric patients have not been established.

Geriatric Use

Of the total number of subjects in clinical studies of pamidronate disodium, approximately 20% were 65 and over, while approximately 15% were 75 and over. No overall differences in safety or effectiveness were observed between these subjects and younger subjects, and other reported clinical experience has not identified differences in responses between the elderly and younger patients, but greater sensitivity of some older individuals cannot be ruled out. In general, dose selection for an elderly patient should be cautious, usually starting at the low end of the dosing range, reflecting the greater frequency of decreased hepatic, renal, or cardiac function, and of concomitant disease or other drug therapy.

ADVERSE REACTIONS

Because clinical trials are conducted under widely varying conditions, adverse reaction rates observed in the clinical trials of a drug cannot be directly compared to rates in the clinical trials of another drug and may not reflect the rates observed in practice.

Clinical Studies

Hypercalcemia of Malignancy

Transient mild elevation of temperature by at least 1°C was noted 24 to 48 hours after administration of pamidronate disodium in 34% of patients in clinical trials. In the saline trial, 18% of patients had a temperature elevation of at least 1°C 24 to 48 hours after treatment.

Drug-related local soft-tissue symptoms (redness, swelling or induration and pain on palpation) at the site of catheter insertion were most common in patients treated with 90 mg of pamidronate disodium. Symptomatic treatment resulted in rapid resolution in all patients.

Rare cases of uveitis, iritis, scleritis, and episcleritis have been reported, including one case of scleritis, and one case of uveitis upon separate rechallenges.

Five of 231 patients (2%) who received pamidronate disodium during the four U.S. controlled hypercalcemia clinical studies were reported to have had seizures, 2 of whom had preexisting seizure disorders. None of the seizures were considered to be drug-related by the investigators. However, a possible relationship between the drug and the occurrence of seizures cannot be ruled out. It should be noted that in the saline arm 1 patient (4%) had a seizure.

There are no controlled clinical trials comparing the efficacy and safety of 90 mg pamidronate disodium over 24 hours to 2 hours in patients with hypercalcemia of malignancy. However, a comparison of data from separate clinical trials suggests that the overall safety profile in patients who received 90 mg pamidronate disodium over 24 hours is similar to those who received 90 mg pamidronate disodium over 2 hours. The only notable differences observed were an increase in the proportion of patients in the pamidronate disodium 24-hour group who experienced fluid overload and electrolyte/mineral abnormalities.

At least 15% of patients treated with pamidronate disodium for hypercalcemia of malignancy also experienced the following adverse events during a clinical trial:

General: Fluid overload, generalized pain

Cardiovascular: Hypertension

Gastrointestinal: Abdominal pain, anorexia, constipation, nausea, vomiting

Genitourinary: Urinary tract infection

Musculoskeletal: Bone pain

Laboratory Abnormality: Anemia, hypokalemia, hypomagnesemia, hypophosphatemia.

Many of these adverse experiences may have been related to the underlying disease state. The following table lists the adverse experiences considered to be treatment-related during comparative, controlled U.S. trials.

Treatment-Related Adverse Experiences Reported in Three U.S. Controlled Clinical Trials
 | Percent of Patients Pamidronate Disodium |  |  | Etidronate Disodium | Saline
 | 60 mg over 4 hr | 60 mg over 24 hr | 90 mg over 24 hr | 7.5 mg/kg × 3 days
 | n=23 | n=73 | n=17 | n=35 | n=23
General
Edema | 0 | 1 | 0 | 0 | 0
Fatigue | 0 | 0 | 12 | 0 | 0
Fever | 26 | 19 | 18 | 9 | 0
Fluid overload | 0 | 0 | 0 | 6 | 0
Infusion-site reaction | 0 | 4 | 18 | 0 | 0
Moniliasis | 0 | 0 | 6 | 0 | 0
Rigors | 0 | 0 | 0 | 0 | 4
Gastrointestinal
Abdominal pain | 0 | 1 | 0 | 0 | 0
Anorexia | 4 | 1 | 12 | 0 | 0
Constipation | 4 | 0 | 6 | 3 | 0
Diarrhea | 0 | 1 | 0 | 0 | 0
Dyspepsia | 4 | 0 | 0 | 0 | 0
Gastrointestinal hemorrhage | 0 | 0 | 6 | 0 | 0
Nausea | 4 | 0 | 18 | 6 | 0
Stomatitis | 0 | 1 | 0 | 3 | 0
Vomiting | 4 | 0 | 0 | 0 | 0
Respiratory
Dyspnea | 0 | 0 | 0 | 3 | 0
Rales | 0 | 0 | 6 | 0 | 0
Rhinitis | 0 | 0 | 6 | 0 | 0
Upper respiratory infection | 0 | 3 | 0 | 0 | 0
CNS
Anxiety | 0 | 0 | 0 | 0 | 4
Convulsions | 0 | 0 | 0 | 3 | 0
Insomnia | 0 | 1 | 0 | 0 | 0
Nervousness | 0 | 0 | 0 | 0 | 4
Psychosis | 4 | 0 | 0 | 0 | 0
Somnolence | 0 | 1 | 6 | 0 | 0
Taste perversion | 0 | 0 | 0 | 3 | 0
Cardiovascular
Atrial fibrillation | 0 | 0 | 6 | 0 | 4
Atrial flutter | 0 | 1 | 0 | 0 | 0
Cardiac failure | 0 | 1 | 0 | 0 | 0
Hypertension | 0 | 0 | 6 | 0 | 4
Syncope | 0 | 0 | 6 | 0 | 0
Tachycardia | 0 | 0 | 6 | 0 | 4
Endocrine
Hypothyroidism | 0 | 0 | 6 | 0 | 0
Hemic and Lymphatic
Anemia | 0 | 0 | 6 | 0 | 0
Leukopenia | 4 | 0 | 0 | 0 | 0
Neutropenia | 0 | 1 | 0 | 0 | 0
Thrombocytopenia | 0 | 1 | 0 | 0 | 0
Musculoskeletal
Myalgia | 0 | 1 | 0 | 0 | 0
Urogenital
Uremia | 4 | 0 | 0 | 0 | 0
Laboratory Abnormalities
Hypocalcemia | 0 | 1 | 12 | 0 | 0
Hypokalemia | 4 | 4 | 18 | 0 | 0
Hypomagnesemia | 4 | 10 | 12 | 3 | 4
Hypophosphatemia | 0 | 9 | 18 | 3 | 0
Abnormal liver function | 0 | 0 | 0 | 3 | 0

Paget’s Disease

Transient mild elevation of temperature >1°C above pretreatment baseline was noted within 48 hours after completion of treatment in 21% of the patients treated with 90 mg of pamidronate disodium in clinical trials.

Drug-related musculoskeletal pain and nervous system symptoms (dizziness, headache, paresthesia, increased sweating) were more common in patients with Paget’s disease treated with 90 mg of pamidronate disodium than in patients with hypercalcemia of malignancy treated with the same dose.

Adverse experiences considered to be related to trial drug, which occurred in at least 5% of patients with Paget’s disease treated with 90 mg of pamidronate disodium in two U.S. clinical trials, were fever, nausea, back pain, and bone pain.

At least 10% of all pamidronate disodium-treated patients with Paget’s disease also experienced the following adverse experiences during clinical trials:

Cardiovascular: Hypertension

Musculoskeletal: Arthrosis, bone pain

Nervous system: Headache

Most of these adverse experiences may have been related to the underlying disease state.

Osteolytic Bone Metastases of Breast Cancer and Osteolytic Lesions of Multiple Myeloma

The most commonly reported (>15%) adverse experiences occurred with similar frequencies in the pamidronate disodium and placebo treatment groups, and most of these adverse experiences may have been related to the underlying disease state or cancer therapy.

Commonly Reported Adverse Experiences in Three U.S. Controlled Clinical Trials
 | Pamidronate Disodium 90 mg over 4 hours | Placebo | Pamidronate Disodium 90 mg over 2 hours | Placebo | All Pamidronate Disodium 90 mg | Placebo
 | N=205 | N=187 | N=367 | N=386 | N=572 | N=573
General | % | % | % | % | % | %
Asthenia | 16.1 | 17.1 | 25.6 | 19.2 | 22.2 | 18.5
Fatigue | 31.7 | 28.3 | 40.3 | 28.8 | 37.2 | 29.0
Fever | 38.5 | 38 | 38.1 | 32.1 | 38.5 | 34
Metastases | 1.0 | 3.0 | 31.3 | 24.4 | 20.5 | 17.5
Pain | 13.2 | 11.8 | 15.0 | 18.1 | 14.3 | 16.1
Digestive System
Anorexia | 17.1 | 17.1 | 31.1 | 24.9 | 26.0 | 22.3
Constipation | 28.3 | 31.7 | 36.0 | 38.6 | 33.2 | 35.1
Diarrhea | 26.8 | 26.8 | 29.4 | 30.6 | 28.5 | 29.7
Dyspepsia | 17.6 | 13.4 | 18.3 | 15.0 | 22.6 | 17.5
Nausea | 35.6 | 37.4 | 63.5 | 59.1 | 53.5 | 51.8
Pain abdominal | 19.5 | 16.0 | 24.3 | 18.1 | 22.6 | 17.5
Vomiting | 16.6 | 19.8 | 46.3 | 39.1 | 35.7 | 32.8
Hemic and Lymphatic
Anemia | 47.8 | 41.7 | 39.5 | 36.8 | 42.5 | 38.4
Granulocytopenia | 20.5 | 15.5 | 19.3 | 20.5 | 19.8 | 18.8
Thrombocytopenia | 16.6 | 17.1 | 12.5 | 14.0 | 14.0 | 15.0
Musculoskeletal System
Arthralgias | 10.7 | 7.0 | 15.3 | 12.7 | 13.6 | 10.8
Myalgia | 25.4 | 15.0 | 26.4 | 22.5 | 26 | 20.1
Skeletal Pain | 61.0 | 71.7 | 70.0 | 75.4 | 66.8 | 74
CNS
Anxiety | 7.8 | 9.1 | 18.0 | 16.8 | 14.3 | 14.3
Headache | 24.4 | 19.8 | 27.2 | 23.6 | 26.2 | 22.3
Insomnia | 17.1 | 17.2 | 25.1 | 19.4 | 22.2 | 19.0
Respiratory System
Coughing | 26.3 | 22.5 | 25.3 | 19.7 | 25.7 | 20.6
Dyspnea | 22.0 | 21.4 | 35.1 | 24.4 | 30.4 | 23.4
Pleural effusion | 2.9 | 4.3 | 15.0 | 9.1 | 10.7 | 7.5
Sinusitis | 14.6 | 16.6 | 16.1 | 10.4 | 15.6 | 12.0
Upper respiratory Tract Infection | 32.2 | 28.3 | 19.6 | 20.2 | 24.1 | 22.9
Urogenital System
Urinary Tract Infection | 15.6 | 9.1 | 20.2 | 17.6 | 18.5 | 15.6

Of the toxicities commonly associated with chemotherapy, the frequency of vomiting, anorexia, and anemia were slightly more common in the pamidronate disodium patients whereas stomatitis and alopecia occurred at a frequency similar to that in placebo patients. In the breast cancer trials, mild elevations of serum creatinine occurred in 18.5% of pamidronate disodium patients and 12.3% of placebo patients. Mineral and electrolyte disturbances, including hypocalcemia, were reported rarely and in similar percentages of pamidronate disodium-treated patients compared with those in the placebo group. The reported frequencies of hypocalcemia, hypokalemia, hypophosphatemia, and hypomagnesemia for pamidronate disodium-treated patients were 3.3%, 10.5%, 1.7%, and 4.4%, respectively, and for placebo-treated patients were 1.2%, 12%, 1.7%, and 4.5%, respectively. In previous hypercalcemia of malignancy trials, patients treated with pamidronate disodium (60 or 90 mg over 24 hours) developed electrolyte abnormalities more frequently (see ADVERSE REACTIONS, Hypercalcemia of Malignancy).

Arthralgias and myalgias were reported slightly more frequently in the pamidronate disodium group than in the placebo group (13.6% and 26% vs 10.8% and 20.1%, respectively).

In multiple myeloma patients, there were five pamidronate disodium-related serious and unexpected adverse experiences. Four of these were reported during the 12-month extension of the multiple myeloma trial. Three of the reports were of worsening renal function developing in patients with progressive multiple myeloma or multiple myeloma-associated amyloidosis. The fourth report was the adult respiratory distress syndrome developing in a patient recovering from pneumonia and acute gangrenous cholecystitis. One pamidronate disodium-treated patient experienced an allergic reaction characterized by swollen and itchy eyes, runny nose, and scratchy throat within 24 hours after the sixth infusion.

In the breast cancer trials, there were four pamidronate disodium-related adverse experiences, all moderate in severity, that caused a patient to discontinue participation in the trial. One was due to interstitial pneumonitis, another to malaise and dyspnea. One pamidronate disodium patient discontinued the trial due to a symptomatic hypocalcemia. Another pamidronate disodium patient discontinued therapy due to severe bone pain after each infusion, which the investigator felt was trial-drug-related.

Renal Toxicity

In a study of the safety and efficacy of pamidronate disodium 90 mg (2 hour infusion) versus Zometa® 4 mg (15 minute infusion) in bone metastases patients with multiple myeloma or breast cancer, renal deterioration was defined as an increase in serum creatinine of 0.5 mg/dL for patients with normal baseline creatinine (<1.4 mg/dL) or an increase of 1.0 mg/dL for patients with an abnormal baseline creatinine (≥ 1.4 mg/dL). The following are data on the incidence of renal deterioration in patients in this trial. See table below.

Incidence of Renal Function Deterioration in Multiple Myeloma and Breast Cancer Patients with Normal and Abnormal Serum Creatinine at Baseline [Patients were randomized following the 15-minute infusion amendment for the Zometa® arm. Zometa® is a registered trademark of Novartis.]
Patient Population/Baseline Creatinine | Pamidronate Disodium 90 mg/2 hours |  | Zometa® 4 mg/15 minutes
 | n/N | (%) | n/N | (%)
Normal | 20/246 | (8.1%) | 23/246 | (9.3%)
Abnormal | 2/22 | (9.1%) | 1/26 | (3.8%)
Total | 22/268 | (8.2%) | 24/272 | (8.8%)

Post-Marketing Experience

The following adverse reactions have been reported during post-approval use of pamidronate disodium. Because these reports are from a population of uncertain size and are subject to confounding factors, it is not possible to reliably estimate their frequency or establish a causal relationship to drug exposure.

The following adverse reactions have been reported in post-marketing use: General: reactivation of Herpes simplex and Herpes zoster, influenza-like symptoms; CNS: confusion and visual hallucinations, sometimes in the presence of electrolyte imbalance; Skin: rash, pruritus; Special senses: conjunctivitis, orbital inflammation; Renal and urinary disorders: focal segmental glomerulosclerosis including the collapsing variant, nephrotic syndrome; renal tubular disorders (RTD); tubulointerstitial nephritis, and glomerulonephropathies. Laboratory abnormalities: hyperkalemia, hypernatremia, hematuria. Rare instances of allergic manifestations have been reported, including hypotension, dyspnea, or angioedema, and, very rarely, anaphylactic shock. Pamidronate disodium is contraindicated in patients with clinically significant hypersensitivity to pamidronate disodium or other bisphosphonates (see CONTRAINDICATIONS.) Respiratory, thoracic and mediastinal disorders: adult respiratory distress syndrome (ARDS), interstitial lung disease (ILD). Musculoskeletal and connective tissue disorders: severe and occasionally incapacitating bone, joint, and/or muscle pain.

Cases of osteonecrosis (primarily involving the jaw) have been reported predominantly in cancer patients treated with intravenous bisphosphonates, including pamidronate disodium. Many of these patients were also receiving chemotherapy and corticosteroids which may be risk factors for ONJ. Data suggest a greater frequency of reports of ONJ in certain cancers, such as advanced breast cancer and multiple myeloma. The majority of the reported cases are in cancer patients following invasive dental procedures, such as tooth extraction. It is therefore prudent to avoid invasive dental procedures as recovery may be prolonged (See PRECAUTIONS).

Atypical subtrochanteric and diaphyseal femoral fractures have been reported with bisphosphonate therapy, including pamidronate disodium (See PRECAUTIONS).

OVERDOSAGE

There have been several cases of drug maladministration of intravenous pamidronate disodium in hypercalcemia patients with total doses of 225 mg to 300 mg given over 2½ to 4 days. All of these patients survived, but they experienced hypocalcemia that required intravenous and/or oral administration of calcium. Single doses of pamidronate disodium should not exceed 90 mg and the duration of the intravenous infusion should be no less than 2 hours (See WARNINGS).

In addition, one obese woman (95 kg) who was treated with 285 mg of pamidronate disodium/day for 3 days experienced high fever (39.5°C), hypotension (from 170/90 mmHg to 90/60 mmHg), and transient taste perversion, noted about 6 hours after the first infusion. The fever and hypotension were rapidly corrected with steroids.

If overdosage occurs, symptomatic hypocalcemia could also result; such patients should be treated with short-term intravenous calcium.

DOSAGE AND ADMINISTRATION

Hypercalcemia of Malignancy

Consideration should be given to the severity of as well as the symptoms of hypercalcemia. Vigorous saline hydration alone may be sufficient for treating mild, asymptomatic hypercalcemia.

Overhydration should be avoided in patients who have potential for cardiac failure. In hypercalcemia associated with hematologic malignancies, the use of glucocorticoid therapy may be helpful.

Moderate Hypercalcemia

The recommended dose of pamidronate disodium in moderate hypercalcemia (corrected serum calcium* of approximately 12 to 13.5 mg/dL) is 60 to 90 mg given as a SINGLE DOSE, intravenous infusion over 2 to 24 hours. Longer infusions (i.e., >2 hours) may reduce the risk for renal toxicity, particularly in patients with preexisting renal insufficiency.

Severe Hypercalcemia

The recommended dose of pamidronate disodium in severe hypercalcemia (corrected serum calcium* >13.5 mg/dL) is 90 mg given as a SINGLE DOSE, intravenous infusion over 2 to 24 hours. Longer infusions (i.e., >2 hours) may reduce the risk for renal toxicity, particularly in patients with preexisting renal insufficiency.

* Albumin-corrected serum calcium (CCa, mg/dL) = serum calcium, mg/dL + 0.8 (4.0-serum albumin, g/dL).

Retreatment

A limited number of patients have received more than one treatment with pamidronate disodium for hypercalcemia. Retreatment with pamidronate disodium, in patients who show complete or partial response initially, may be carried out if serum calcium does not return to normal or remain normal after initial treatment. It is recommended that a minimum of 7 days elapse before retreatment, to allow for full response to the initial dose. The dose and manner of retreatment is identical to that of the initial therapy.

Paget’s Disease

The recommended dose of pamidronate disodium in patients with moderate to severe Paget’s disease of bone is 30 mg daily, administered as a 4-hour infusion on 3 consecutive days for a total dose of 90 mg.

Retreatment

A limited number of patients with Paget’s disease have received more than one treatment of pamidronate disodium in clinical trials. When clinically indicated, patients should be retreated at the dose of initial therapy.

Osteolytic Bone Lesions of Multiple Myeloma

The recommended dose of pamidronate disodium in patients with osteolytic bone lesions of multiple myeloma is 90 mg administered as a 4-hour infusion given on a monthly basis.

Patients with marked Bence-Jones proteinuria and dehydration should receive adequate hydration prior to pamidronate disodium infusion.

Limited information is available on the use of pamidronate disodium in multiple myeloma patients with a serum creatinine ≥ 3.0 mg/dL.

Patients who receive pamidronate disodium should have serum creatinine assessed prior to each treatment. Treatment should be withheld for renal deterioration. In a clinical study, renal deterioration was defined as follows:

For patients with normal baseline creatinine, increase of 0.5 mg/dL.
For patients with abnormal baseline creatinine, increase of 1.0 mg/dL.

In this clinical study, pamidronate disodium treatment was resumed only when the creatinine returned to within 10% of the baseline value.

The optimal duration of therapy is not yet known, however, in a study of patients with myeloma, final analysis after 21 months demonstrated overall benefits (see Clinical Trials section).

Osteolytic Bone Metastases of Breast Cancer

The recommended dose of pamidronate disodium in patients with osteolytic bone metastases is 90 mg administered over a 2-hour infusion given every 3 to 4 weeks.

Pamidronate disodium has been frequently used with doxorubicin, fluorouracil, cyclophosphamide, methotrexate, mitoxantrone, vinblastine, dexamethasone, prednisone, melphalan, vincristine, megesterol, and tamoxifen. It has been given less frequently with etoposide, cisplatin, cytarabine, paclitaxel, and aminoglutethimide.

Patients who receive pamidronate disodium should have serum creatinine assessed prior to each treatment. Treatment should be withheld for renal deterioration. In a clinical study, renal deterioration was defined as follows:

For patients with normal baseline creatinine, increase of 0.5 mg/dL.
For patients with abnormal baseline creatinine, increase of 1.0 mg/dL.

In this clinical study, pamidronate disodium treatment was resumed only when the creatinine returned to within 10% of the baseline value.

The optimal duration of therapy is not known, however, in two breast cancer studies, final analyses performed after 24 months of therapy demonstrated overall benefits (see Clinical Trials section).

Calcium and Vitamin D Supplementation

In the absence of hypercalcemia, patients with predominantly lytic bone metastases or multiple myeloma, who are at risk of calcium or vitamin D deficiency, and patients with Paget’s disease of the bone, should be given oral calcium and vitamin D supplementation in order to minimize the risk of hypocalcemia.

Method of Administration

DUE TO THE RISK OF CLINICALLY SIGNIFICANT DETERIORATION IN RENAL FUNCTION, WHICH MAY PROGRESS TO RENAL FAILURE, SINGLE DOSES OF PAMIDRONATE DISODIUM SHOULD NOT EXCEED 90 MG (SEE WARNINGS).

There must be strict adherence to the intravenous administration recommendations for pamidronate disodium in order to decrease the risk of deterioration in renal function.

Hypercalcemia of Malignancy

The daily dose must be administered as an intravenous infusion over at least 2 to 24 hours for the 60 mg and 90-mg doses. The recommended dose should be diluted in 1000 mL of sterile 0.45% or 0.9% Sodium Chloride, USP, or 5% Dextrose Injection, USP. This infusion solution is stable for up to 24 hours at room temperature.

Paget’s Disease

The recommended daily dose of 30 mg should be diluted in 500 mL of sterile 0.45% or 0.9% Sodium Chloride, USP, or 5% Dextrose Injection, USP, and administered over a 4-hour period for 3 consecutive days.

Osteolytic Bone Metastases of Breast Cancer

The recommended dose of 90 mg should be diluted in 250 mL of sterile 0.45% or 0.9% Sodium Chloride, USP, or 5% Dextrose Injection, USP, and administered over a 2-hour period every 3 to 4 weeks.

Osteolytic Bone Lesions of Multiple Myeloma

The recommended dose of 90 mg should be diluted in 500 mL of sterile 0.45% or 0.9% Sodium Chloride, USP, or 5% Dextrose Injection, USP, and administered over a 4-hour period on a monthly basis.

Pamidronate disodium must not be mixed with calcium-containing infusion solutions, such as Ringer’s solution, and should be given in a single intravenous solution and line separate from all other drugs. Note: Parenteral drug products should be inspected visually for particulate matter and discoloration prior to administration, whenever solution and container permit.

HOW SUPPLIED

Vials – 3 mg/mL, 10 mL vial - each contains 30 mg of Pamidronate Disodium and 470 mg of Mannitol, USP in 10 mL Water for Injection, USP.

Unit of Sale | Concentration
NDC 61703-324-18 Carton of 1 Single-dose vial | 30 mg/10 mL (3 mg/mL)

Vials – 6 mg/mL, 10 mL vial - each contains 60 mg of Pamidronate Disodium and 400 mg of Mannitol, USP in 10 mL Water for Injection, USP.

Unit of Sale | Concentration
NDC 61703-325-18 Carton of 1 Single-dose vial | 60 mg/10 mL (6 mg/mL)

Vials – 9 mg/mL, 10 mL vial - each contains 90 mg of Pamidronate Disodium and 375 mg of Mannitol, USP in 10 mL Water for Injection, USP.

Unit of Sale | Concentration
NDC 61703-326-18 Carton of 1 Single-dose vial | 90 mg/10 mL (9 mg/mL)

Store at 20 to 25°C (68 to 77°F) [see USP Controlled Room Temperature].

Distributed by Hospira, Inc.,
Lake Forest, IL 60045 USA

LAB-1156-3.0

Revised: 4/2021

PRINCIPAL DISPLAY PANEL - 60 mg/10 mL Vial Label

Sterile
NDC 61703-325-18
10 mL Single-dose Vial
Rx only

Pamidronate Disodium
Injection

60 mg/ 10 mL
(6 mg/mL)

Do not mix with calcium containing infusion solutions
For Intravenous Infusion

PRINCIPAL DISPLAY PANEL - 60 mg/10 mL Vial Carton

VIAL
Hospira

1 x 10 mL Vial
NDC 61703-325-18
Sterile
Rx only

Pamidronate
Disodium
Injection

60 mg/ 10 mL
(6 mg/mL)

Do not mix with calcium
containing infusion solutions

For Intravenous Infusion

Single-dose Vial

PRINCIPAL DISPLAY PANEL - 90 mg/10 mL Vial Label

Sterile
NDC 61703-326-18
10 mL Single-dose Vial
Rx only

Pamidronate Disodium
Injection

90 mg/ 10 mL
(9 mg/mL)

Do not mix with calcium containing infusion solutions
For Intravenous Infusion

PRINCIPAL DISPLAY PANEL - 90 mg/10 mL Vial Carton

VIAL
Hospira

1 x 10 mL Vial
NDC 61703-326-18
Sterile
Rx only

Pamidronate
Disodium
Injection

90 mg/ 10 mL
(9 mg/mL)

Do not mix with calcium
containing infusion solutions

For Intravenous Infusion

Single-dose Vial

PRINCIPAL DISPLAY PANEL - 30 mg/10 mL Vial Label

Sterile
NDC 61703-324-18
10 mL Single-dose Vial
Rx only

Pamidronate Disodium
Injection

30 mg/ 10 mL
(3 mg/mL)

Do not mix with calcium containing infusion solutions
For Intravenous Infusion

PRINCIPAL DISPLAY PANEL - 30 mg/10 mL Vial Carton

VIAL
Hospira

1 x 10 mL Vial
NDC 61703-324-18
Sterile
Rx only

Pamidronate
Disodium
Injection

30 mg/ 10 mL
(3 mg/mL)

Do not mix with calcium
containing infusion solutions

For Intravenous Infusion

Single-dose Vial